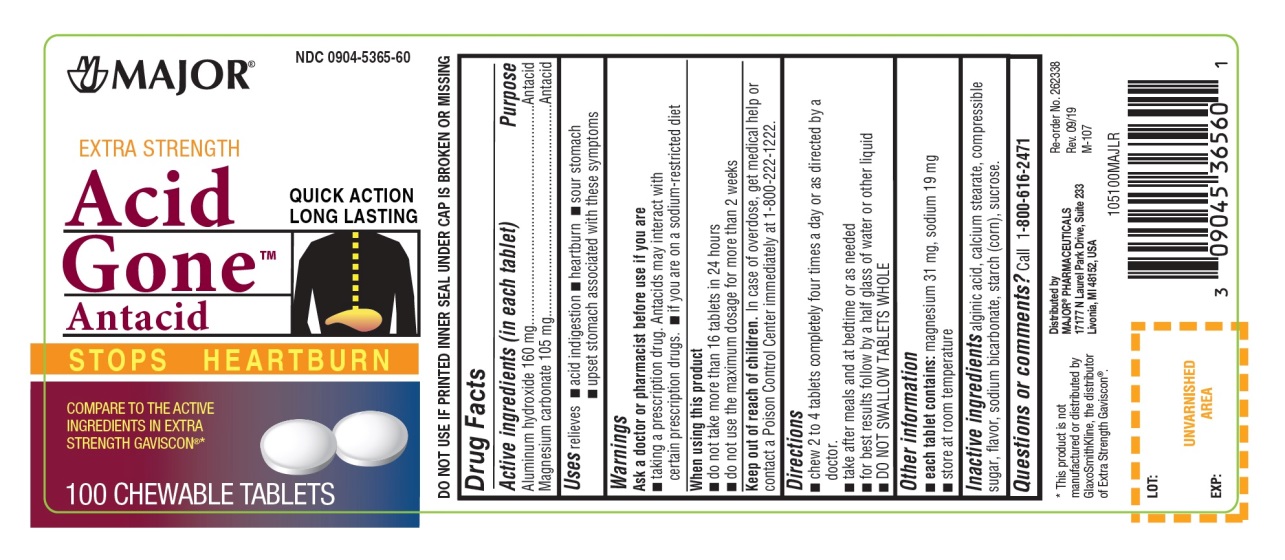 DRUG LABEL: Acid Gone Antacid

NDC: 0904-5365 | Form: TABLET, CHEWABLE
Manufacturer: Major Pharmaceuticals
Category: otc | Type: HUMAN OTC DRUG LABEL
Date: 20250919

ACTIVE INGREDIENTS: ALUMINUM HYDROXIDE 160 mg/1 1; MAGNESIUM CARBONATE 105 mg/1 1
INACTIVE INGREDIENTS: ALGINIC ACID; CALCIUM STEARATE; CORN SYRUP; SODIUM BICARBONATE; STARCH, CORN; SUCROSE

Extra Strength Acid Gone Antacid 100 Chewable Tablets Drug Facts

Active ingredients (in each tablet)

Aluminum hydroxide 160mg

Magnesium carbonate 105mg

Purpose

Antacid

Uses

relieves

- acid indigestion
- heartburn
- sour stomach
- upset stomach associated with these symptoms

Warnings

Ask a doctor or pharmacist before use if you are

- taking a prescription drug. Antacids may interact with certain prescription drugs.
- if you are on a sodium-restricted diet

When using this product

- do not take more than 16 tablets in 24 hours
- do not use the maximum dosage for more than 2 weeks

Keep out of reach of children.

In case of overdose, get medical help or contact a Poison Control Center immediately at 1-800-222-1222.

Directions

- chew 2-4 tablets four times a day or as directed by a doctor
- take after meals and at bedtime or as needed
- for best results follow by a half glass of water or other liquid
- DO NOT SWALLOW TABLET WHOLE

Other information

- Each tablet contains :sodium 19 mg, magnesium 31mg
- Store at room temperature

Inactive ingredients

alginic acid, calcium stearate, compressible sugar, flavor, sodium bicarbonate, starch(corn), sucrose.

Questions or comments?

call 1-800-616-2471

Principal Display Panel

NDC 0904-5365-60

EXTRA STRENGTH

Acid Gone™

Antacid

STOPS HEARTBURN

QUICK ACTION

LONG LASTING

COMPARE TO THE ACTIVE INGREDIENT IN EXTRA STRENGTH GAVISCON®*

100 CHEWABLE TABLETS

Distributed by:

MAJOR®PHARMACEUTICALS

17177 N Laurel Park Drive, Suite 233

Livonia, MI 48150, USA

*This product is not manufactured or distributed by GlaxoSmithKline, the distributor of Extra Strength Gaviscon®